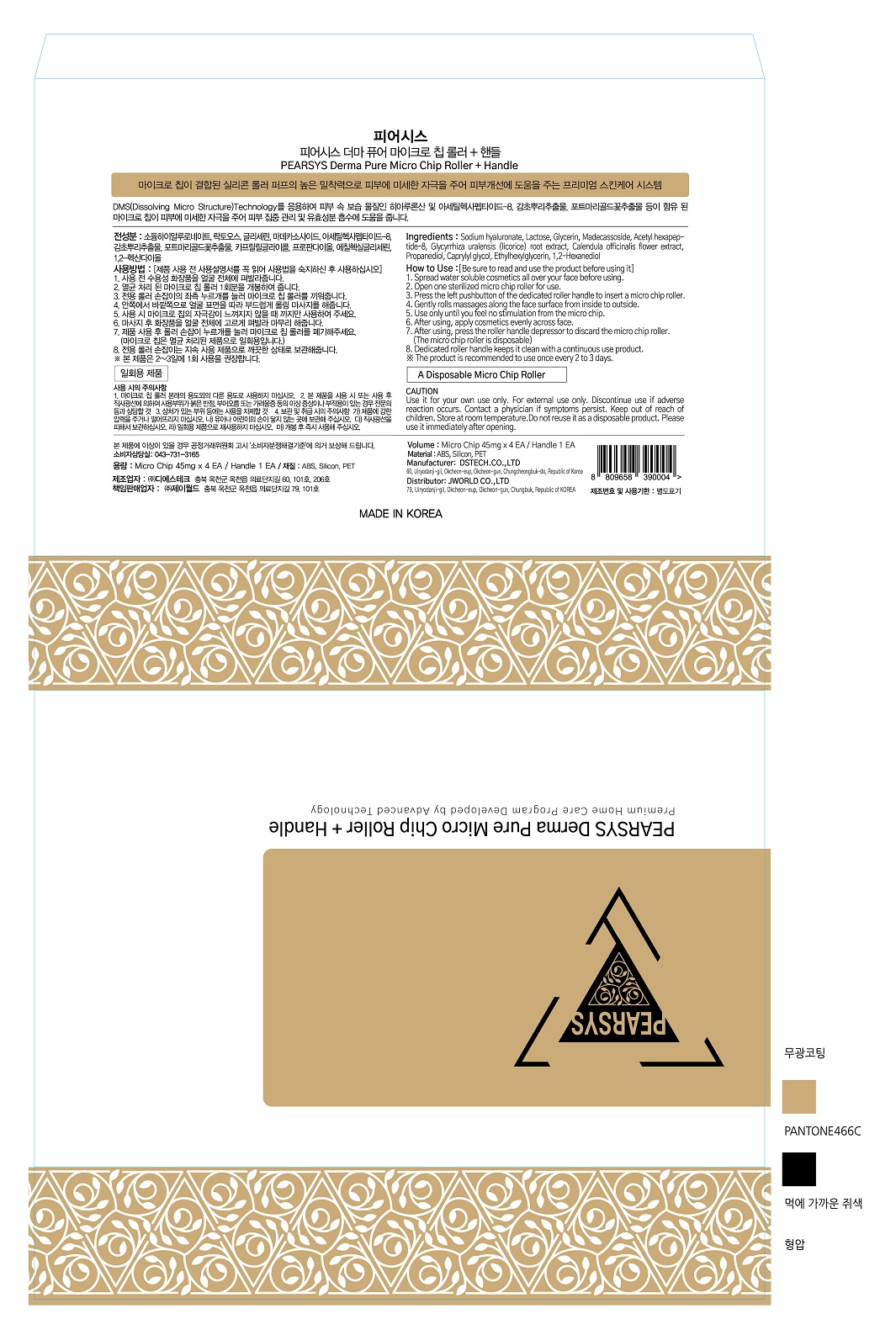 DRUG LABEL: PEARSYS
NDC: 72945-0003 | Form: PATCH
Manufacturer: J World
Category: otc | Type: HUMAN OTC DRUG LABEL
Date: 20211201

ACTIVE INGREDIENTS: HYALURONATE SODIUM 6.14 g/100 g
INACTIVE INGREDIENTS: ACETYL HEXAPEPTIDE-8

Drug Facts

ACTIVE INGREDIENT

Sodium hyaluronate

INACTIVE INGREDIENT

Water
Caprylyl glycol
Acetyl hexapeptide-8

Cellulose gum
Lactose
Glycerin

Calendula officinalis flower extract
1,2-Hexanediol

Glycyrrhiza uralensis (licorice) root extract
Propanediol
Ethylhexyl glycerin
Madecassoside

PURPOSE

DMS (Dissolving Micro Structure) Technology Microchip gives minute skin stimulation to help skin concentrate and absorb active ingredients

keep out of reach of the children

INDICATIONS AND USAGE

spread water soluble cosmetics all over your face before using

open one sterilized micro chip roller for use

press the left pushbutton of the dedicated roller handle to insert a micro chip roller

gently rolls massages along the fact surface from inside to outside

use only until you feel no stimulation from the micro chip

after using, apply cosmetics evenly across face

after using, press the roller handle depressor to discard the micro chip roller (the micro chip roller is disposable)

dedicated roller handle keeps it clean with a continous use product

(this product is recommended to use one every 2 to 3 days)

WARNINGS

Use it for your own use only.

For external use only.

Discontinue use if adverse reaction occurs.

Contact a physician if symptoms persist.

Store at room temperature

.Do not reuse it as a disposable product.

Please use it immediately after opening.

DOSAGE AND ADMINISTRATION

for topical use only